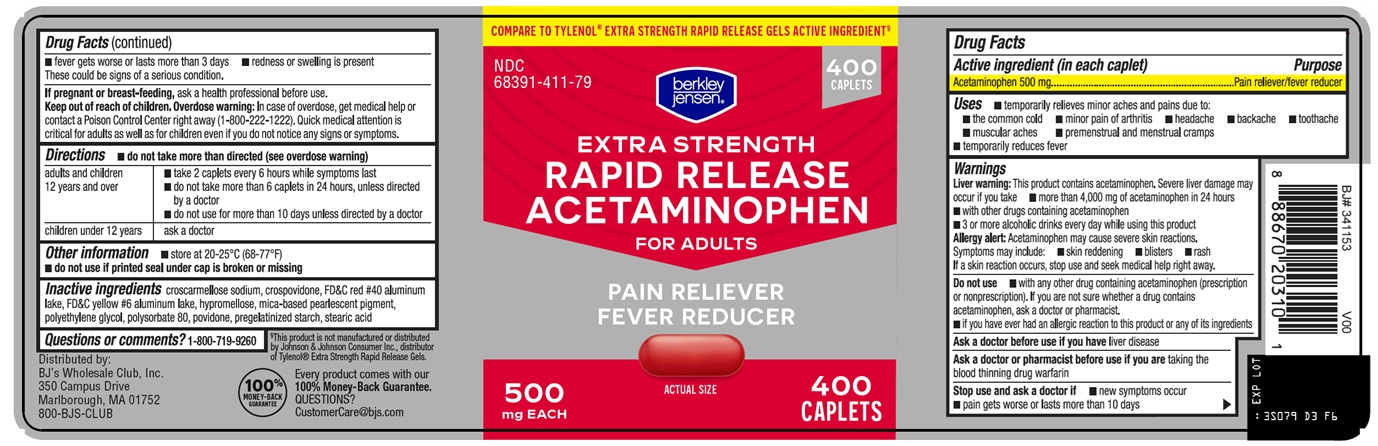 DRUG LABEL: BERKLEY AND JENSEN RAPID RELEASE ACETAMINOPHEN
NDC: 68391-411 | Form: TABLET, FILM COATED
Manufacturer: BJWC
Category: otc | Type: HUMAN OTC DRUG LABEL
Date: 20251208

ACTIVE INGREDIENTS: ACETAMINOPHEN 500 mg/1 1
INACTIVE INGREDIENTS: CROSCARMELLOSE SODIUM; CROSPOVIDONE, UNSPECIFIED; FD&C RED NO. 40 ALUMINUM LAKE; FD&C YELLOW NO. 6 ALUMINUM LAKE; HYPROMELLOSE, UNSPECIFIED; POLYETHYLENE GLYCOL, UNSPECIFIED; POLYSORBATE 80; POVIDONE, UNSPECIFIED; STEARIC ACID

BJWC Rapid Release Acetaminophen Drug Facts

Active ingredient (in each caplet)

Acetaminophen 500 mg

Purpose

Pain reliever/fever reducer

Uses

- temporarily relieves minor aches and pains due to:
  - the common cold
  - minor pain of arthritis
  - headache
  - backache
  - toothache
  - muscular aches
  - premenstrual and menstrual cramps
- temporarily reduces fever

Warnings

Liver warning: This product contains acetaminophen. Severe liver damage may occur if you take

- more than 4,000 mg of acetaminophen in 24 hours
- with other drugs containing acetaminophen
- 3 or more alcoholic drinks every day while using this product

Allergy alert: Acetaminophen may cause severe skin reactions. Symptoms may include:

- skin reddening
- blisters
- rash

If a skin reaction occurs, stop use and seek medical help right away.

Do not use

- with any other drug containing acetaminophen (prescription or nonprescription). If you are not sure whether a drug contains acetaminophen, ask a doctor or pharmacist.
- if you have ever had an allergic reaction to this product or any of its ingredients

Ask a doctor before use if you have

liver disease

Ask a doctor or pharmacist before use if you are

taking the blood thinning drug warfarin

Stop use and ask a doctor if

- new symptoms occur
- pain gets worse or lasts more than 10 days
- fever gets worse or lasts more than 3 days
- redness or swelling is present

These could be signs of a serious condition.

If pregnant or breast-feeding,

ask a health professional before use.

Keep out of reach of children.

Overdose warning: In case of overdose, get medical help or contact a Poison Control Center right away (1-800-222-1222). Quick medical attention is critical for adults as well as for children even if you do not notice any signs or symptoms.

Directions

- do not take more than directed (see overdose warning)

adults and children 12 years and over | - take 2 caplets every 6 hours while symptoms last - do not take more than 6 caplets in 24 hours, unless directed by a doctor - do not use for more than 10 days unless directed by a doctor
children under; 12 years | ask a doctor

Other information

- store at 20-25°C (68-77°F)
- do not use if printed seal under cap is broken or missing

Inactive ingredients

croscarmellose sodium, crospovidone, FD&C red #40 aluminum lake, FD&C yellow #6 aluminum lake, hypromellose, mica-based pearlescent pigment, polyethylene glycol, polysorbate 80, povidone, pregelatinized starch, stearic acid

Questions or comments?

1-800-719-9260

Package/Label Principal Display Panel

COMPARE TO TYLENOL® EXTRA STRENGTH RAPID RELEASE GELS ACTIVE INGREDIENT

400 CAPLETS

berkley jensen®

EXTRA STRENGTH

RAPID RELEASE ACETAMINOPHEN

FOR ADULTS

PAIN RELIEVER

FEVER REDUCER

ACTUAL SIZE

500 mg EACH

400 CAPLETS